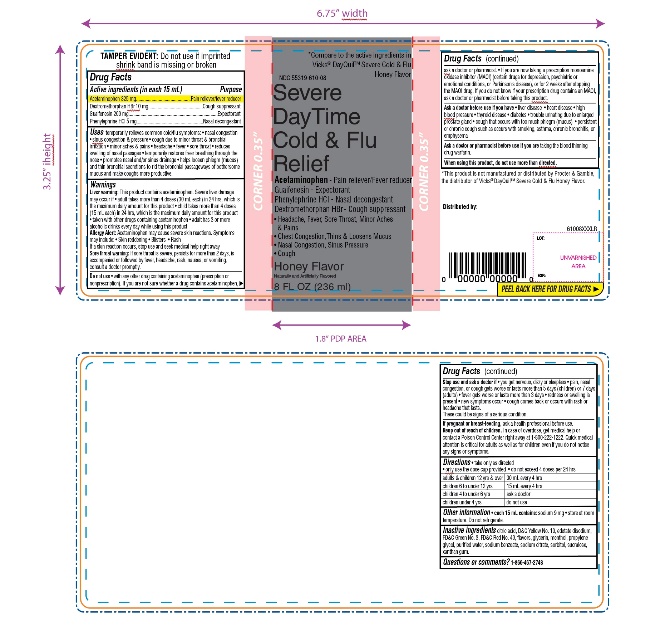 DRUG LABEL: DayTime Severe Cold and Flu Relief
NDC: 55319-061 | Form: LIQUID
Manufacturer: FAMILY DOLLAR SERVICES INC
Category: otc | Type: HUMAN OTC DRUG LABEL
Date: 20230725

ACTIVE INGREDIENTS: ACETAMINOPHEN 325 mg/15 mL; DEXTROMETHORPHAN HYDROBROMIDE 10 mg/15 mL; PHENYLEPHRINE HYDROCHLORIDE 5 mg/15 mL; GUAIFENESIN 200 mg/15 mL
INACTIVE INGREDIENTS: CITRIC ACID MONOHYDRATE; D&C YELLOW NO. 10; EDETATE DISODIUM; FD&C GREEN NO. 3; FD&C RED NO. 40; GLYCERIN; MENTHOL, UNSPECIFIED FORM; PROPYLENE GLYCOL; WATER; SODIUM BENZOATE; SODIUM CITRATE, UNSPECIFIED FORM; SORBITOL; SUCRALOSE; XANTHAN GUM

DayTime Severe Cold & Flu Relief Honey Flavor

Drug Facts

Active ingredients (in each 15 mL)

Acetaminophen 325 mg

Dextromethorphan HBr 10 mg

Guaifenesin 200 mg

Phenylephrine HCl 5 mg

Purpose

Pain reliever/fever reducer
Cough suppressant

Expectorant

Nasal decongestant

Uses

temporarily relieves common cold/flu symptoms:

- nasal congestion
- sinus congestion & pressure
- cough due to minor throat & bronchial irritation
- minor aches & pains
- headache
- fever
- sore throat
- reduces swelling of nasal passages
- temporarily restores freer breathing through the nose
- promotes nasal and/or sinus drainage
- helps loosen phlegm (mucus) and thin bronchial secretions to rid the bronchial passageways of bothersome mucus and make coughs more productive.

Warnings

Liver warning

This product contains acetaminophen. Severe liver damage may occur if

- adult takes more than 4 doses (30 mL each) in 24 hrs, which is the maximum daily amount for this product
- child takes more than 4 doses (15 mL each) in 24 hrs, which is the maximum daily amount for this product
- taken with other drugs containing acetaminophen
- adult has 3 or more alcoholic drinks every day while using this product

Allergy Alert:

Acetaminophen may cause severe skin reactions. Symptoms may include:

- Skin reddening
- Blisters
- Rash

If a skin reaction occurs, stop use and seek medical help right away

Sore throat warning

If sore throat is severe, persists for more than 2 days, is accompanied or is followed by fever, headache, rash, nausea, or vomiting, consult a doctor promptly.

Do not use

- with any other drug containing acetaminophen (prescription or nonprescription). If you are not sure whether a drug contains acetaminophen, ask a doctor or pharmacist.
- if you are now taking a prescription monoamine oxidase inhibitor (MAOI) (certain drugs for depression, psychiatric or emotional conditions, or Parkinson's disease), or for 2 weeks after stopping the MAOI drug. If you do not know if your prescription drug contains an MAOI, ask a doctor or pharmacist before taking this product.

Ask a doctor before use if you have

- liver disease
- heart disease
- high blood pressure
- thyroid disease
- diabetes
- trouble urinating due to enlarged prostate gland
- cough that occurs with too much phlegm (mucus)
- persists or chronic cough such as occurs with smoking, asthma, chronic bronchitis, or emphysema

Ask a doctor or pharmacist before use if you are

taking the blood thinning drug warfarin

When using this product,

do not use more than directed

Stop use and ask a doctor if

- you get nervous, dizzy or sleepless
- pain, nasal congestion or cough gets worse or lasts more than 5 days (children) 7 days (adults)
- fever gets worse or lasts more than 3 days
- redness or swelling is present
- new symptoms occur
- cough comes back or occurs with rash or headache that lasts.
  These could be signs of a serious condition.

PREGNANCY OR BREAST FEEDING

If pregnant or breast-feeding, ask a health professional before use.

Keep out of reach of children.

In case of overdose, get medical help or contact a Poison Control Center right away at 1-800-222-1222. Quick medical attention is critical for adults as well as for children even if you do not notice any signs or symptoms.

Directions

- take only as directed
- only use the dose cup provided
- do not exceed 4 doses per 24 hrs

adults & children 12 yrs & over | 30 mL every 4 hrs
children 6 to under 12 yrs | 15 mL every 4 hrs
children 4 to under 6 yrs | ask a doctor
children under 4 yrs | do not use

Other information

- each 15 mL contains: sodium 9 mg
- Store at room temperature
- Do not refrigerate.

Inactive ingredients

citric acid, D&C Yellow No. 10, edetate disodium, FD&C Green No. 3, FD&C Red No. 40, flavors, glycerin, menthol, propylene glycol, purified water, sodium benzoate, sodium citrate, sorbitol, sucralose, xanthan gum

Questions?

1-866-467-2748

*This product is not manufactured or distributed by Procter & Gamble, distributer of Vicks® Dayquil™ Severe Cold & Flu Honey Flavor

Distributed. by:

PRINCIPAL DISPLAY PANEL - 354 mL Bottle Label

*Compare to the active ingredients in Vicks® DayQuil™ Severe Cold & Flu Honey Flavor

NDC 55319-061-08

DayTime

Severe

Cold & Flu

Relief

Acetaminophen – Pain reliever/Fever reducer

Guaifenesin – Expectorant

Phenylephrine HCl - Nasal decongestant

Dextromethorphan HBr – Cough suppressant

- Headache, Fever, Sore Throat, Minor Aches & Pains
- Chest Congestion, Thins & Loosens Mucus
- Nasal Congestion, Sinus Pressure
- Cough

Honey Flavor

Naturally and Artificially Flavored

8 FL OZ (236 ml)